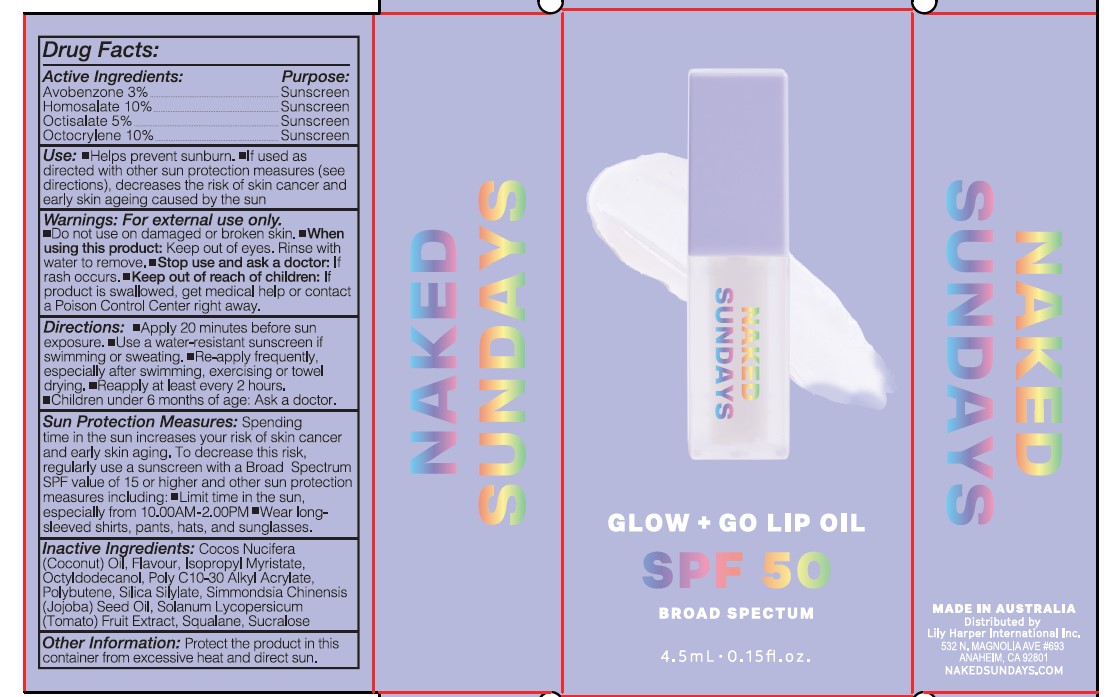 DRUG LABEL: Glow Go Lip Oil
NDC: 30807-7000 | Form: OIL
Manufacturer: WILD CHILD LABORATORIES PTY LTD
Category: otc | Type: HUMAN OTC DRUG LABEL
Date: 20250728

ACTIVE INGREDIENTS: HOMOSALATE 10 g/100 mL; OCTISALATE 5 g/100 mL; OCTOCRYLENE 10 g/100 mL; AVOBENZONE 3 g/100 mL
INACTIVE INGREDIENTS: ISOPROPYL MYRISTATE; SODIUM BENZOATE; CITRULLUS LANATUS WHOLE; PHENOXYETHANOL; POLYBUTENE (1400 MW); OCTYLDODECANOL

NAKED SUNDAYS Glow + Go Lip Oil SPF50 BROAD SPECTRUM COCO CLEAR

ACTIVE INGREDIENTS

AVOBENZONE 3 %

HOMOSALATE 10%

OCTISALATE 5 %

OCTOCRYLENE 10%

PURPOSE

SUNSCREEN

USE

- Helps prevents sunburn

- If used as directed with other sun protection measures (see directions) decreases the risk of skin cancer and early skin ageing caused by the sun.

WARNINGS

FOR EXTERNAL USE ONLY

- Do not use on damaged or broken skin.

WHEN USING

keep out of eyes, Rinse with water to remove

Stop use & ask doctor

If rash occurs

KEEP OUT OF REACH OF CHILDREN

If product is swallowed , get medical help or contact a poison control center right away

Directions

- Apply 20 minutes before sun exposure

- Use a water resistant sunscreen if swimming or sweating

- Re-apply frequently especially after swimming excercising or towel drying

- Re-apply at least every 2 hours

- Children under 6 months of age- ask a doctor

Sun Protection Measures :

Spending time in the sun increases your risk of skin cancer and early skin aging. To decrease this risk, regularly use a sunscreen with a Broad spectrum SPF value of 15 or higher and other sun protection measures inclusing:

- limit time in the sun, especially from 10:00 AM- 02:00 PM

- Wear long- Sleeved shirts , pants, Hats and sunglasses

Inactive Ingredients

Citrullus Lanatus Seed oil, Flavor, Isopropyl myristate, Octyldodecanol, Phenoxyethanol, Polybutene, Sodium Benzoate

OTHER SAFETY INFORMATION

Protect the product in this container from excessive heat & direct sun